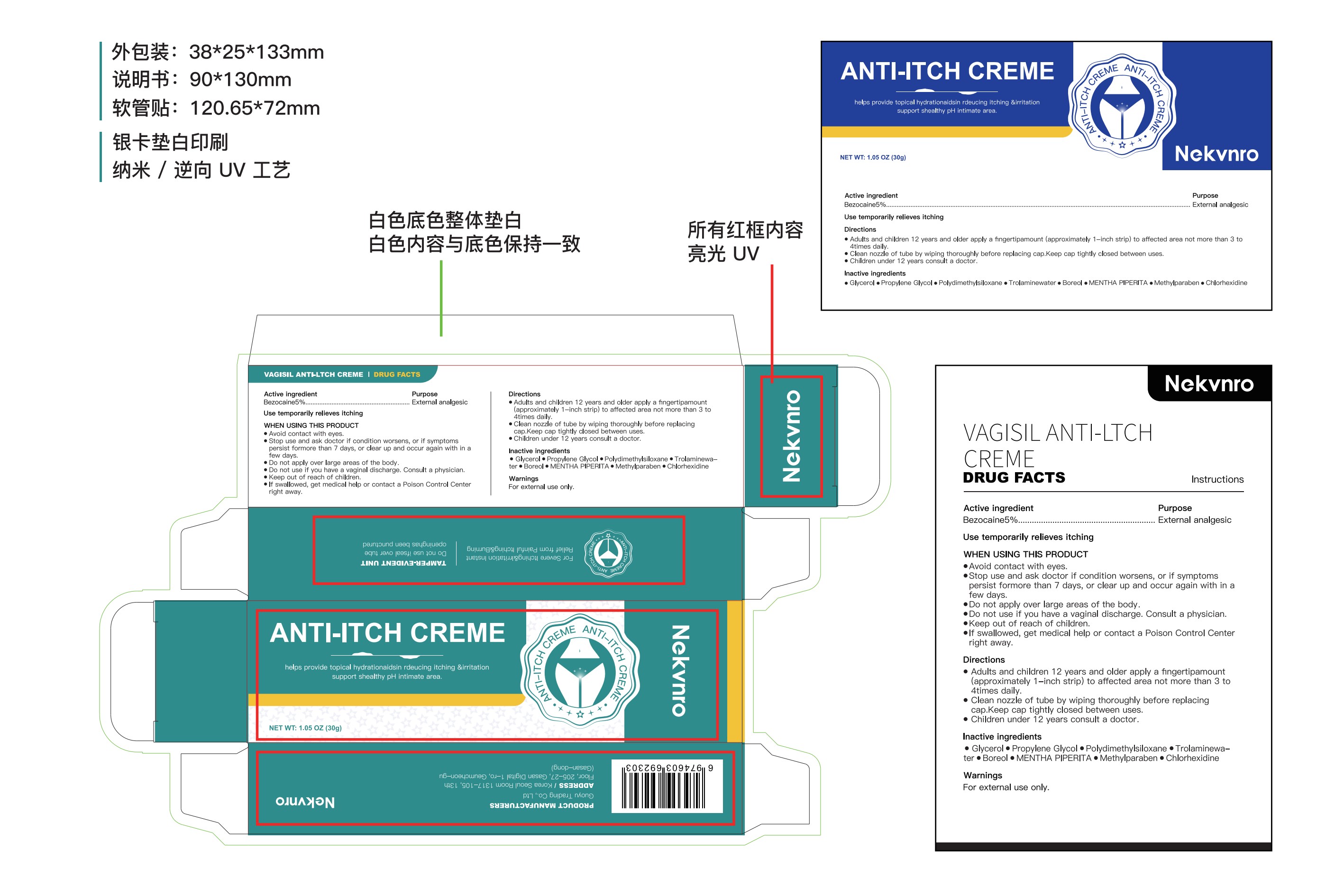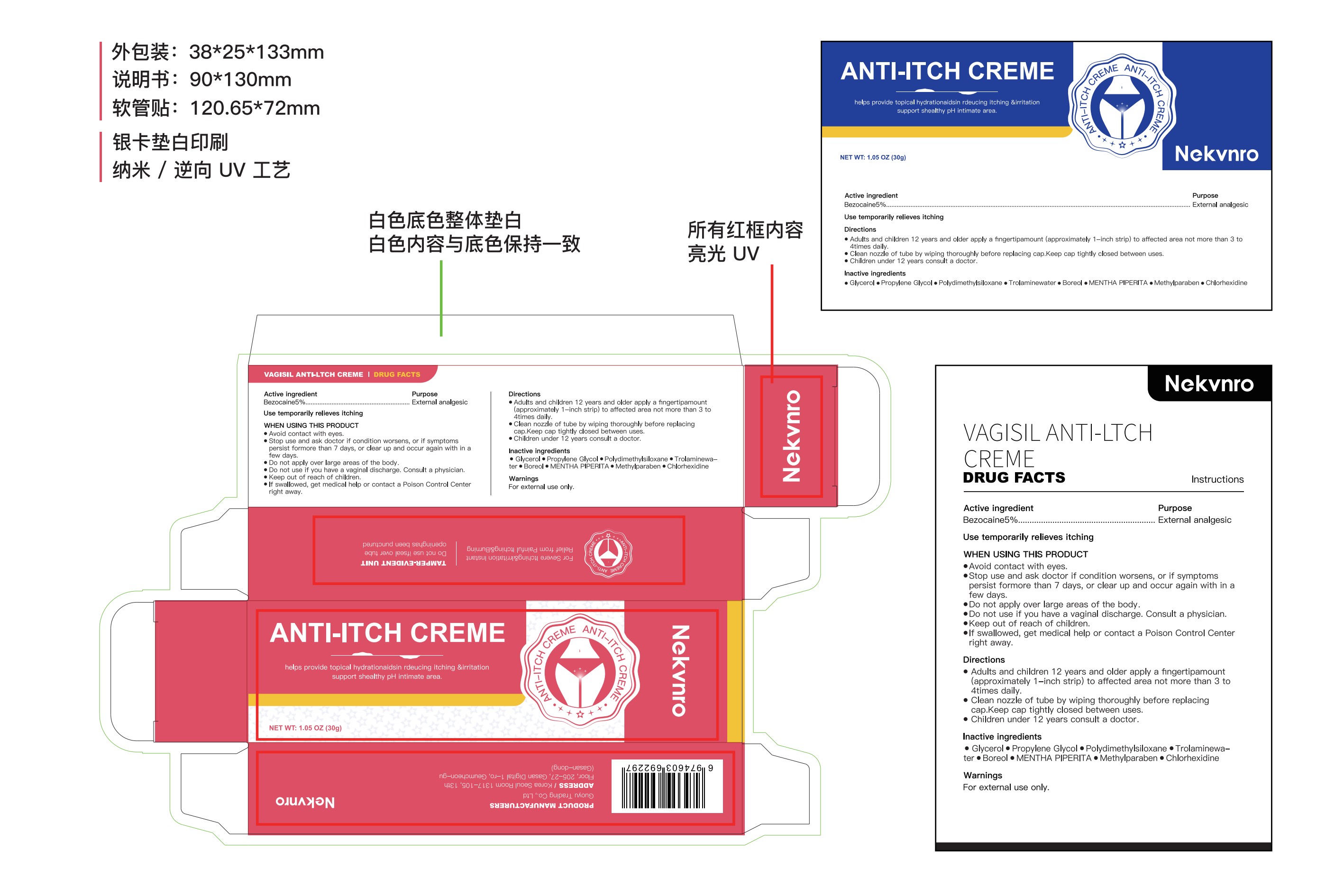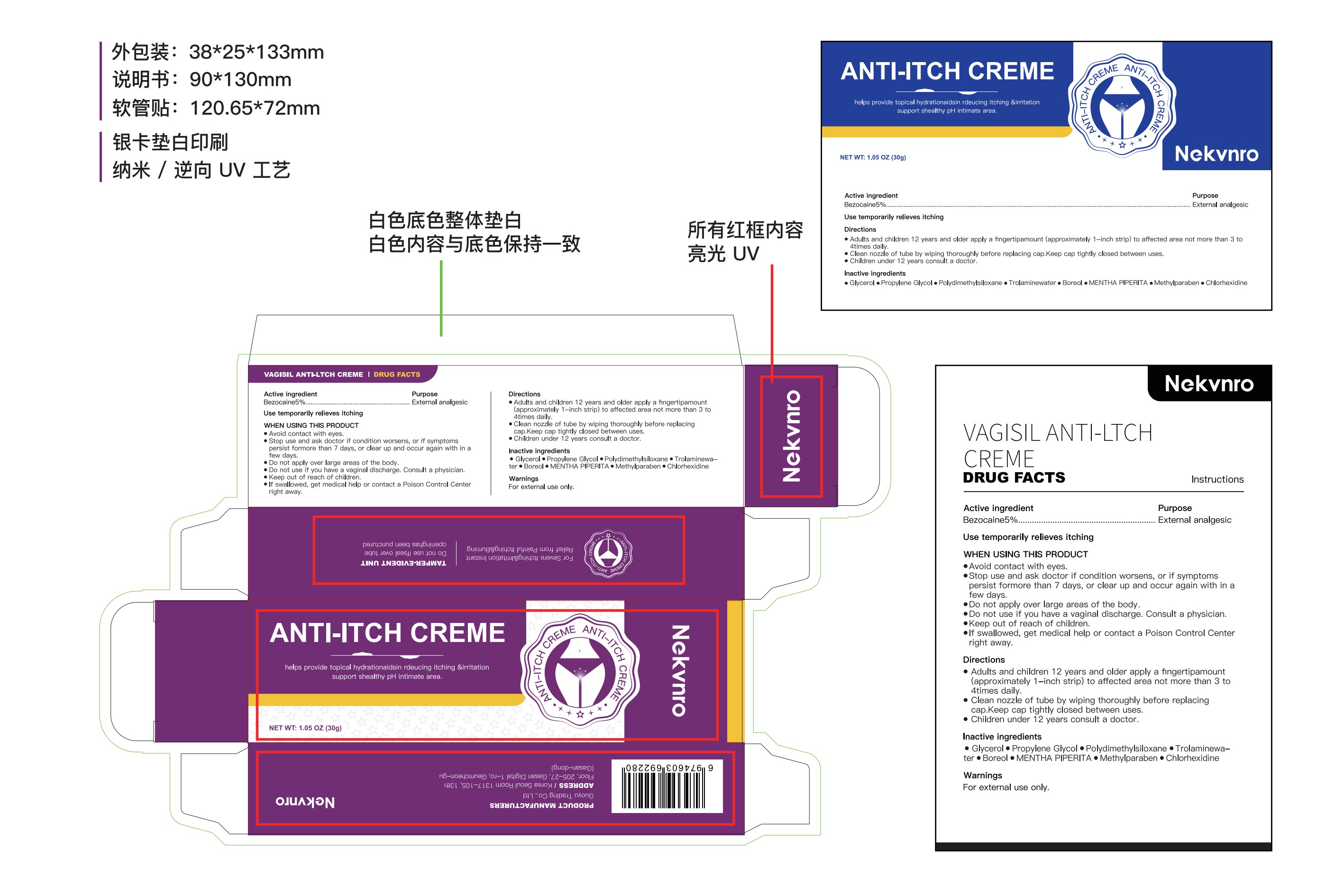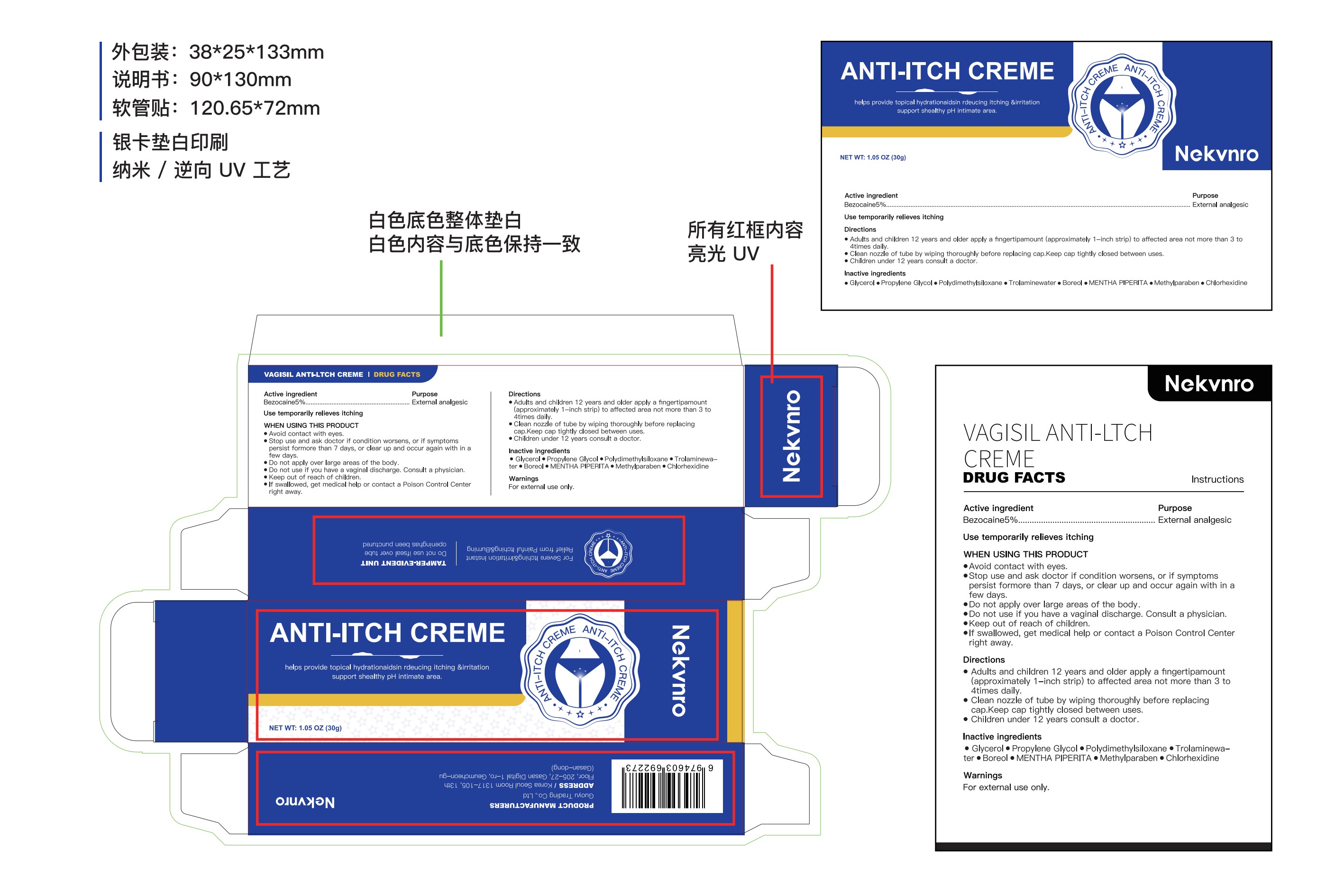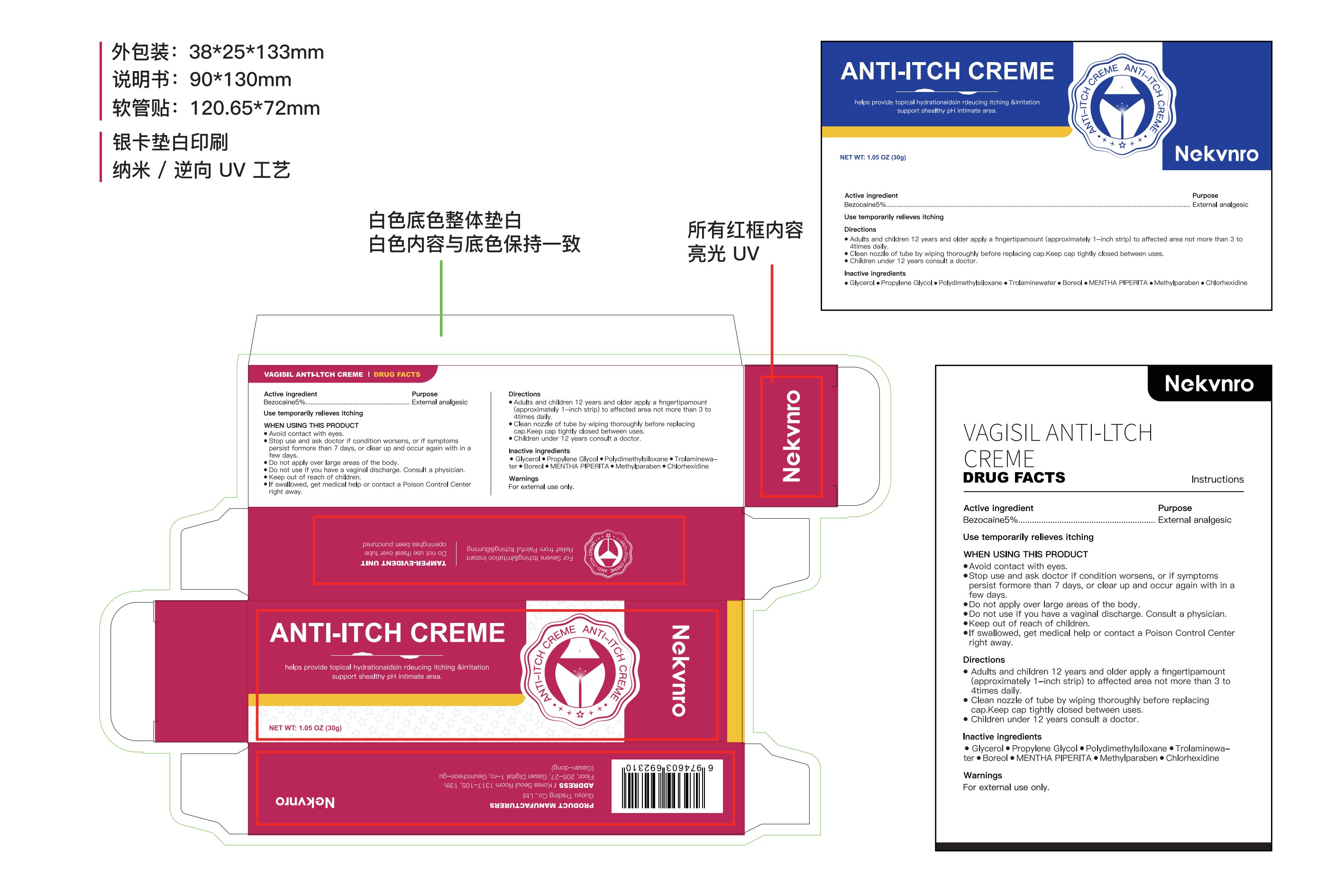 DRUG LABEL: Nekvnro Anti-Itch Creme
NDC: 84844-007 | Form: CREAM
Manufacturer: Guoyu Trading Co., Ltd.
Category: otc | Type: HUMAN OTC DRUG LABEL
Date: 20241031

ACTIVE INGREDIENTS: BEZLOTOXUMAB 5 g/100 g
INACTIVE INGREDIENTS: TROLAMINE; PROPYLENE GLYCOL; CHLORHEXIDINE; METHYLPARABEN; GLYCERIN; DIMETHICONE; BOROFALAN B-10; MENTHA PIPERITA

84844-007

Active Ingredient

Bezocaine 5%

Purpose

External analgesic

Use

temporarily relieves itching

Warnings

For external use only

Do not use

Stop use and ask doctor if condition worsens, or if symptoms persist formore than 7 days, or clear up and occur again with in a few daysDo not apply over large areas of the body
Do not use if you have a vaginal discharge. Consult a physician.

When Using

THIS PRODUCT Avoid contact with eyes

Stop Use

Stop use and ask doctor if condition worsens, or if symptoms persist formore than 7 days, or clear up and occur again with in a few daysDo not apply over large areas of the body
Do not use if you have a vaginal discharge. Consult a physician.

Ask Doctor

Stop use and ask doctor if condition worsens, or if symptoms persist formore than 7 days, or clear up and occur again with in a few daysDo not apply over large areas of the body
Do not use if you have a vaginal discharge. Consult a physician.

Keep Oot Of Reach Of Children

lf swallowed, get medical help or contact a Poison Control Center right away.

Directions

adults and children 12 years and older apply a fingertipamount (approximately 1-inch strip) to affected area not more than 3 to 4times daily.Clean nozzle of tube by wiping thoroughly before replacing cap.Keep cap tightly closed between uses.
children under 12 years consult a doctor

Inactive ingredients

Glycerol 、Propylene Glycol 、Polydimethylsiloxane 、Trolaminewater、Boreol 、MENTHA PIPERITA、Methylparaben 、Chlorhexidine